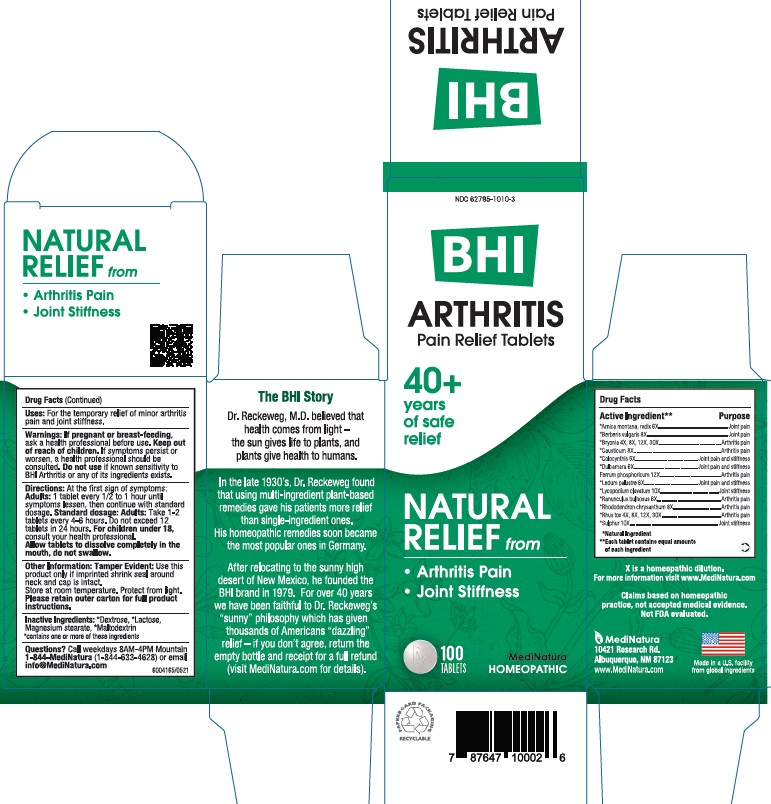 DRUG LABEL: BHI Arthritis
NDC: 62795-1010 | Form: TABLET
Manufacturer: MediNatura Inc
Category: homeopathic | Type: HUMAN OTC DRUG LABEL
Date: 20241217

ACTIVE INGREDIENTS: ARNICA MONTANA ROOT 6 [hp_X]/1 1; BERBERIS VULGARIS ROOT BARK 8 [hp_X]/1 1; BRYONIA ALBA WHOLE 4 [hp_X]/1 1; CAUSTICUM 4 [hp_X]/1 1; CITRULLUS COLOCYNTHIS FRUIT PULP 5 [hp_X]/1 1; SOLANUM DULCAMARA TOP 6 [hp_X]/1 1; FERROSOFERRIC PHOSPHATE 12 [hp_X]/1 1; LEDUM PALUSTRE TWIG 6 [hp_X]/1 1; LYCOPODIUM CLAVATUM SPORE 10 [hp_X]/1 1; RANUNCULUS BULBOSUS 8 [hp_X]/1 1; RHODODENDRON AUREUM LEAF 6 [hp_X]/1 1; TOXICODENDRON PUBESCENS LEAF 4 [hp_X]/1 1; SULFUR 10 [hp_X]/1 1
INACTIVE INGREDIENTS: LACTOSE; MAGNESIUM STEARATE; MALTODEXTRIN; DEXTROSE

BHI Arthritis Tablet

ACTIVE INGREDIENTS

Each tablet contains: *Arnica montana, radix 6X, *Berberis vulgaris 8X, *Bryonia alba 4X, 8X, 12X, 30X, Causticum 8X, *Colocynthis 5X, *Dulcamara 6X, Ferrum phosphoricum 12X, *Ledum palustre 6X, *Lycopodium clavatum 10X, *Ranunculus bulbosus 6X, *Rhododendron chrysanthum 8X, *Rhus toxicodendron 4X, 8X, 12X, 30X, *Sulphur 10X 15.8 mg each.

*Natural Ingredients

INACTIVE INGREDIENTS

Inactive Ingredients: **Dextrose, ** Lactose, Magnesium Stearate, **Maltodextrin
**contains one or more of these ingredients.

PURPOSE

Arthritis Pain Relief Tablets

Relieves:

• Arthritis Pain

• Joint Stiffness

WARNINGS

If pregnant or breast-feeding, ask a health professional before use. Keep out of reach of children. If symptoms persist or worsen, a health professional should be consulted.Do not use if known sensitivity to Arthritis or any of its ingredients exists.

USES

For the temporary relief of minor arthritis pain, joint stiffness.

Directions

At first sign of symptoms: Adults: 1 tablet every 1/2 to 1 hour until symptoms lessen, then continue with standard dosage.

Standard dosage: Adults: Take 1-2 tablets every 4 to 6 hours. Do not exceed 12 tablets in 24 hours.

For children under 18, consult your health professional.

Allow tablets to dissolve completely in the mouth, do not swallow.

KEEP OUT OF REACH OF CHILDREN